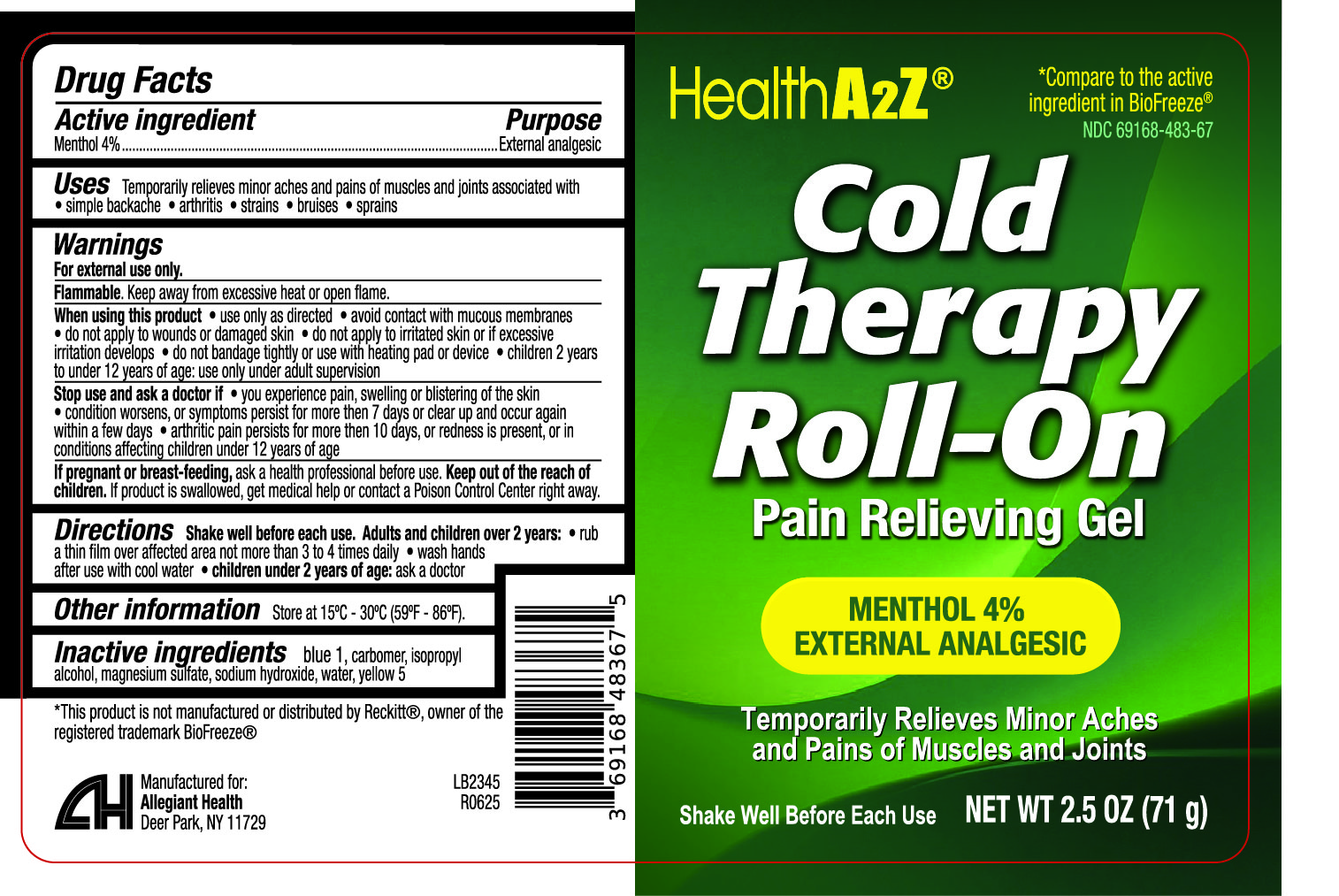 DRUG LABEL: Cold Therapy Roll on
NDC: 69168-483 | Form: GEL
Manufacturer: Allegiant Health
Category: otc | Type: HUMAN OTC DRUG LABEL
Date: 20250729

ACTIVE INGREDIENTS: MENTHOL .04 g/1 mL
INACTIVE INGREDIENTS: BLUE 1; CARBOMER; ISOPROPYL ALCOHOL; MAGNESIUM SULFATE; SODIUM HYDROXIDE; WATER; YELLOW 5

483 - Cold Therapy Roll on

Active ingredient(s)

Menthol 4%

Purpose

Pain Relieving Gel

Use(s)

Temporarily relieves minor aches and pains of muscles and joints associated with:

- simple backache
- arthritis
- strains
- bruises
- sprains

Warnings

For external use only.

Flammable: Keep away from excessive heat or open flame

When using this product

• use only as directed

• avoid contact with mucous membranes

• do not apply to wounds or damaged skin

• do not apply to irritated skin or if excessive irritation develops

• do not bandage tightly or use with heating pad or device

• children 2 years to under 12 years of age: use only under adult supervision

Stop use and ask a doctor if

• you experience pain, swelling or blistering of the skin
• condition worsens, or symptoms persist for more then 7 days or clear up and occur again
within a few days

• arthritic pain persists for more then 10 days, or redness is present, or in
conditions affecting children under 12 years of age

If pregnant or breastfeeding,

ask a health professional before use.

Keep out of reach of children

If product is swallowed, get medical help or contact a Poison Control Center right away.

Directions

Shake well before each use.

Adults and children over 2 years:

• rub a thin film over affected area not more than 3 to 4 times daily

• wash hands after use with cool water

children under 2 years of age: ask a doctor

Other information

Store at 15ºC - 30ºC (59ºF - 86ºF).

Inactive ingredients

blue 1, carbomer, isopropyl alcohol, magnesium sulfate, sodium hydroxide, water, yellow 5

Questions/Comments

Call 1-888-952-0050

(Monday-Friday 9 AM – 5 PM EST)

Principal Display Panel

Cold Therapy Roll on